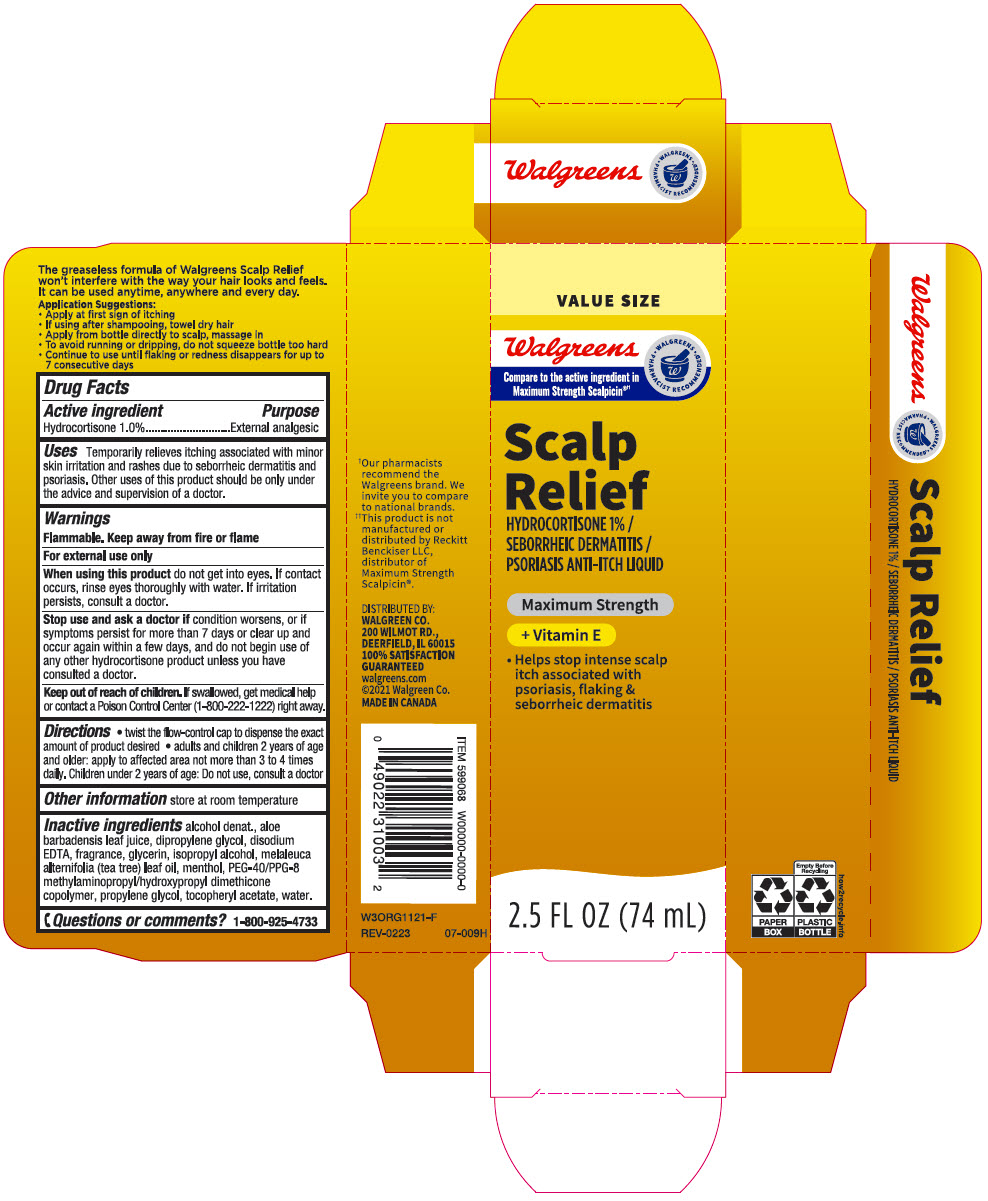 DRUG LABEL: Walgreens Scalp Relief
NDC: 0363-9068 | Form: LIQUID
Manufacturer: Walgreen Company
Category: otc | Type: HUMAN OTC DRUG LABEL
Date: 20240418

ACTIVE INGREDIENTS: HYDROCORTISONE 10 mg/1 mL
INACTIVE INGREDIENTS: ALCOHOL; ALOE VERA LEAF; Dipropylene Glycol; EDETATE DISODIUM; Glycerin; Isopropyl Alcohol; TEA TREE OIL; MENTHOL, UNSPECIFIED FORM; Propylene Glycol; .ALPHA.-TOCOPHEROL ACETATE, DL-; Water

Walgreens Scalp Relief
External analgesic

Drug Facts

Active ingredient

Hydrocortisone 1.0%

Purpose

External analgesic

Uses

Temporarily relieves itching associated with minor skin irritation and rashes due to seborrheic dermatitis and psoriasis. Other uses of this product should be only under the advice and supervision of a doctor.

Warnings

Flammable. Keep away from fire or flame.

For external use only.

When using this product do not get into eyes. If contact occurs, rinse eyes thoroughly with water. If Irritation persists, consult a doctor.

Stop use and consult a doctor if

- condition worsens, or if symptoms persist for more than 7 days or clear up and occur again within a few days, and do not begin use of any other hydrocortisone product unless you have consulted a doctor.

Keep out of reach of children. If swallowed, get medical help or contact a Poison Control Center (1-800-222-1222) right away.

Directions

- twist the flow-control cap to dispense the exact amount of product desired
- adults and children 2 years of age and older: apply to affected area not more than 3 to 4 times daily. Children under 2 years of age: Do not use, consult a doctor.

Other information

store at room temperature

Inactive ingredients

alcohol denat., aloe barbadensis leaf juice, dipropylene glycol, disodium EDTA, fragrance, glycerin, isopropyl alcohol, melaleuca alternifolia (tea tree) leaf oil, menthol, PEG-40/PPG-8 methylaminopropyl/hydroxypropyl dimethicone copolymer, propylene glycol, tocopheryl acetate, water.

Questions or comments?

1-866-925-4733

DISTRIBUTED BY:
WALGREEN CO.
200 WILMOT RD.,
DEERFIELD, IL 60015

PRINCIPAL DISPLAY PANEL - 74 mL Bottle Carton

VALUE SIZE

Walgreens

• WALGREENS •
PHARMACIST RECOMMENDED

Compare to the active ingredient in
Maximum Strength Scalpicin®††

Scalp
Relief

HYDROCORTISONE 1% /
SEBORRHEIC DERMATITIS /
PSORIASIS ANTI-ITCH LIQUID

Maximum Strength

+ Vitamin E

- Helps stop intense scalp
  itch associated with
  psoriasis, flaking &
  seborrheic dermatitis

2.5 FL OZ (74 mL)